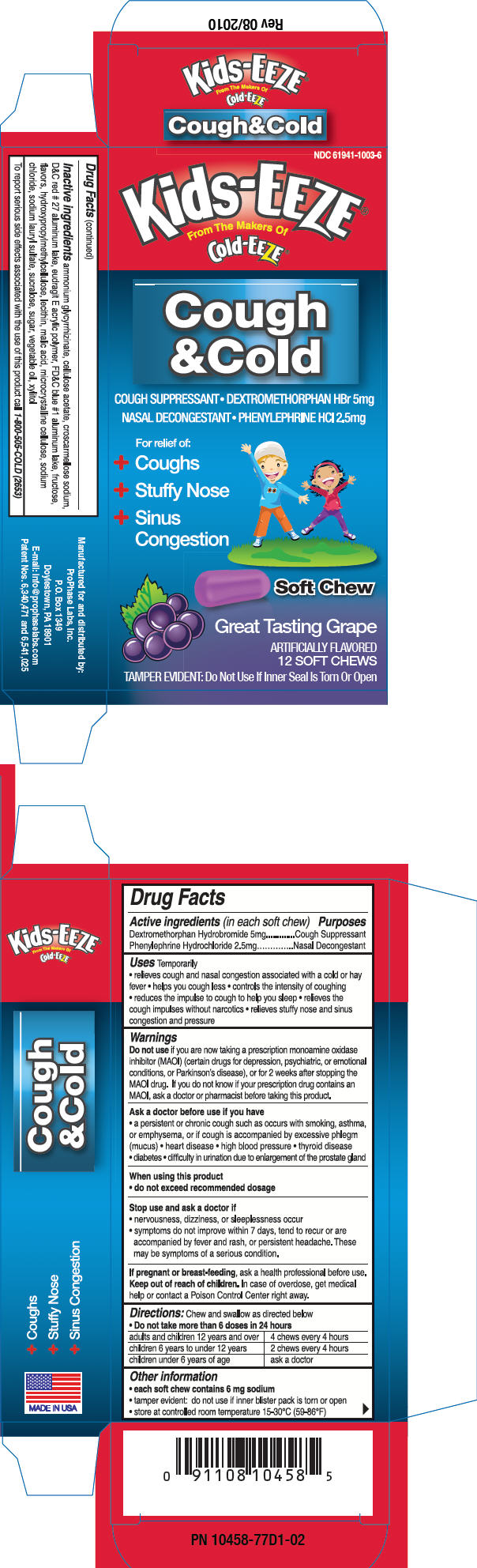 DRUG LABEL: Kids-EEZE 
NDC: 61941-1003 | Form: TABLET, ORALLY DISINTEGRATING
Manufacturer: ProPhase Labs, Inc.
Category: otc | Type: HUMAN OTC DRUG LABEL
Date: 20110401

ACTIVE INGREDIENTS: Dextromethorphan Hydrobromide 5 mg/1 1; Phenylephrine Hydrochloride 2.5 mg/1 1
INACTIVE INGREDIENTS: CROSCARMELLOSE SODIUM; CELLULOSE ACETATE; FRUCTOSE; MALIC ACID; LECITHIN, SOYBEAN; SODIUM CHLORIDE; SODIUM LAURYL SULFATE; XYLITOL

Kids-EEZE®
Cough
& Cold
Soft Chews
Great Tasting Grape

Drug Facts

ACTIVE INGREDIENT

PURPOSE

Active ingredients (in each soft chew) | Purposes
Dextromethorphan Hydrobromide 5mg | Cough Suppressant
Phenylephrine Hydrochloride 2.5mg | Nasal Decongestant

Uses

Temporarily

- relieves cough and nasal congestion associated with a cold or hay fever
- helps you cough less
- controls the intensity of coughing
- reduces the impulse to cough to help you sleep
- relieves the cough impulses without narcotics
- relieves stuffy nose and sinus congestion and pressure

Warnings

Do not use if you are now taking a prescription monoamine oxidase inhibitor (MAOI) (certain drugs for depression, psychiatric, or emotional conditions, or Parkinson's disease), or for 2 weeks after stopping the MAOI drug.

ASK DOCTOR/PHARMACIST

If you do not know if your prescription drug contains an MAOI, ask a doctor or pharmacist before taking this product.

Ask a doctor before use if you have

- a persistent or chronic cough such as occurs with smoking, asthma, or emphysema, or if cough is accompanied by excessive phlegm (mucus)
- heart disease
- high blood pressure
- thyroid disease
- diabetes
- difficulty in urination due to enlargement of the prostate gland

When using this product

- do not exceed recommended dosage

Stop use and ask a doctor if

- nervousness, dizziness, or sleeplessness occur
- symptoms do not improve within 7 days, tend to recur or are accompanied by fever and rash, or persistent headache. These may be symptoms of a serious condition.

PREGNANCY OR BREAST FEEDING

If pregnant or breast-feeding, ask a health professional before use.

Keep out of reach of children. In case of overdose, get medical help or contact a Poison Control Center right away.

Directions

Chew and swallow as directed below

- Do not take more than 6 doses in 24 hours

adults and children 12 years and over | 4 chews every 4 hours
children 6 years to under 12 years | 2 chews every 4 hours
children under 6 years of age | ask a doctor

Other information

- each soft chew contains 6 mg sodium
- tamper evident: do not use if inner blister pack is torn or open
- store at controlled room temperature 15-30°C (59-86°F)

Inactive ingredients

ammonium glycyrrhizinate, cellulose acetate, croscarmellose sodium, D&C red # 27 aluminum lake, eudragit E acrylic polymer, FD&C blue #1 aluminum lake, fructose, flavors, hydroxypropylmethylcellulose, lecithin, malic acid, microcrystalline cellulose, sodium chloride, sodium lauryl sulfate, sucralose, sugar, vegetable oil, xylitol

QUESTIONS

To report serious side effects associated with the use of this product call 1-800-505-COLD (2653)

PRINCIPAL DISPLAY PANEL - 12 SOFT CHEW PACKAGE

NDC 61941-1003-6

Kids-EEZE®
From The Makers Of
Cold-EEZE®

Cough
&Cold

COUGH SUPPRESSANT • DEXTROMETHORPHAN HBr 5mg

NASAL DECONGESTANT • PHENYLEPHRINE HCl 2.5mg

For relief of:

+ Coughs
+ Stuffy Nose
+ Sinus
  Congestion

Soft Chew

Great Tasting Grape

ARTIFICIALLY FLAVORED
12 SOFT CHEWS

TAMPER EVIDENT: Do Not Use If Inner Seal Is Torn Or Open